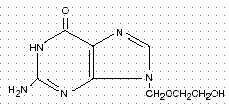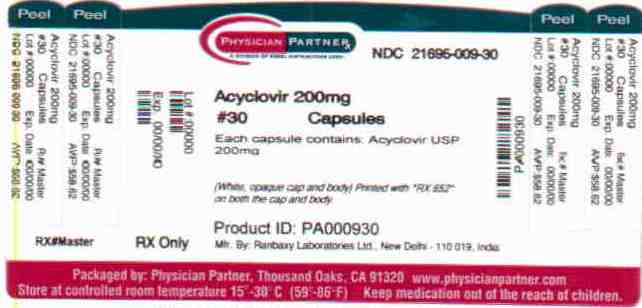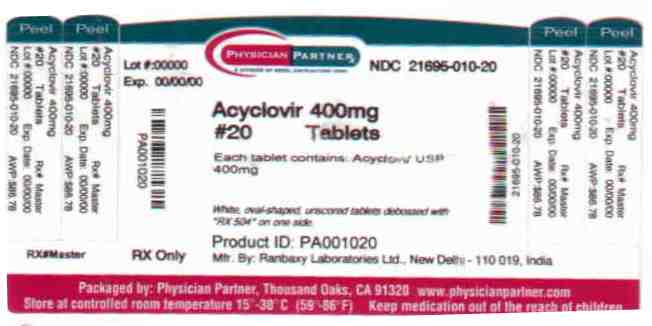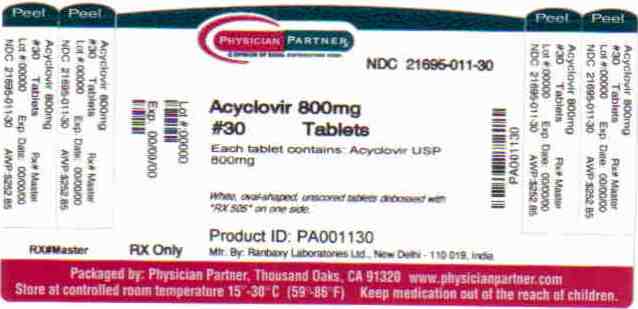 DRUG LABEL: Acyclovir
NDC: 21695-009 | Form: CAPSULE
Manufacturer: Rebel Distributors Corp
Category: prescription | Type: HUMAN PRESCRIPTION DRUG LABEL
Date: 20110105

ACTIVE INGREDIENTS: Acyclovir 200 mg/1 1
INACTIVE INGREDIENTS: lactose monohydrate; magnesium stearate; STARCH, CORN; gelatin; titanium dioxide; FERROSOFERRIC OXIDE

Acyclovir

Rxonly

DESCRIPTION

Acyclovir is a synthetic nucleoside analogue active against herpesviruses. Acyclovir capsules, USP and acyclovir tablets, USP are formulations for oral administration.

Each capsule of acyclovir contains 200 mg of acyclovir, USP and the inactive ingredients lactose monohydrate, magnesium stearate, and pregelatinized starch. The capsule shell consists of black iron oxide, edible printing ink, gelatin, and titanium dioxide.

Each 800 mg tablet of acyclovir contains 800 mg of acyclovir, USP and the inactive ingredients colloidal silicone dioxide, magnesium stearate, microcrystalline cellulose, pregelatinized starch, and sodium starch glycolate.

Each 400 mg tablet of acyclovir contains 400 mg of acyclovir, USP and the inactive ingredients colloidal silicone dioxide, magnesium stearate, microcrystalline cellulose, pregelatinized starch, and sodium starch glycolate.

Acyclovir, USP is a white crystalline powder with the molecular formula C8H11N5O3 and a molecular weight of 225. The maximum solubility in water at 37°C is 2.5 mg/mL.

The pka’s of acyclovir are 2.27 and 9.25. The chemical name of acyclovir is 2-amino-1, 9-dihydro-9-[(2-hydroxyethoxy)methyl]-6H-purin-6-one; it has the following structural formula:

VIROLOGY

Mechanism of Antiviral Action: Acyclovir is a synthetic purine nucleoside analogue with in vitro and in vivo inhibitory activity against herpes simplex virus types 1 (HSV-1), 2 (HSV-2), and varicella-zoster virus (VZV).

The inhibitory activity of acyclovir is highly selective due to its affinity for the enzyme thymidine kinase (TK) encoded by HSV and VZV. This viral enzyme converts acyclovir into acyclovir monophosphate, a nucleotide analogue. The monophosphate is further converted into diphosphate by cellular guanylate kinase and into triphosphate by a number of cellular enzymes. In vitro, acyclovir triphosphate stops replication of herpes viral DNA. This is accomplished in 3 ways: 1) competitive inhibition of viral DNA polymerase, 2) incorporation into and termination of the growing viral DNA chain, and 3) inactivation of the viral DNA polymerase. The greater antiviral activity of acyclovir against HSV compared to VZV is due to its more efficient phosphorylation by the viral TK.

Antiviral Activities: The quantitative relationship between the in vitro susceptibility of herpes viruses to antivirals and the clinical response to therapy has not been established in humans, and virus sensitivity testing has not been standardized. Sensitivity testing results, expressed as the concentration of drug required to inhibit by 50% the growth of virus in cell culture (IC50), vary greatly depending upon a number of factors. Using plaque-reduction assays, the IC50 against herpes simplex virus isolates ranges from 0.02 to 13.5 mcg/mL for HSV-1 and from 0.01 to 9.9 mcg/mL for HSV-2. The IC50 for acyclovir against most laboratory strains and clinical isolates of VZV ranges from 0.12 to 10.8 mcg/mL. Acyclovir also demonstrates activity against the Oka vaccine strain of VZV with a mean IC50 of 1.35 mcg/mL.

Drug Resistance: Resistance of HSV and VZV to acyclovir can result from qualitative and quantitative changes in the viral TK and/or DNA polymerase. Clinical isolates of HSV and VZV with reduced susceptibility to acyclovir have been recovered from immunocompromised patients, especially with advanced HIV infection. While most of the acyclovir-resistant mutants isolated thus far from immunocompromised patients have been found to be TK-deficient mutants, other mutants involving the viral TK gene (TK partial and TK altered) and DNA polymerase have been isolated. TK-negative mutants may cause severe disease in infants and immunocompromised adults. The possibility of viral resistance to acyclovir should be considered in patients who show poor clinical response during therapy.

CLINICAL PHARMACOLOGY

Pharmacokinetics: The pharmacokinetics of acyclovir after oral administration have been evaluated in healthy volunteers and in immunocompromised patients with herpes simplex or varicella-zoster virus infection. Acyclovir pharmacokinetic parameters are summarized in Table 1.

Table 1: Acyclovir Pharmacokinetic Characteristics (Range)
Parameter | Range
Plasma protein binding | 9% to 33%
Plasma elimination half-life | 2.5 to 3.3 hr
Average oral bioavailability | 10% to 20%*
*Bioavailability decreases with increasing dose.

In one multiple-dose, cross-over study in healthy subjects (n = 23), it was shown that increases in plasma acyclovir concentrations were less than dose proportional with increasing dose, as shown in Table 2. The decrease in bioavailability is a function of the dose and not the dosage form.

Table 2: Acyclovir Peak and Trough Concentrations at Steady State
Parameter | 200 mg | 400 mg | 800 mg
C ssmax | 0.83 mcg/mL | 1.21 mcg/mL | 1.61 mcg/mL
C sstrough | 0.46 mcg/mL | 0.63 mcg/mL | 0.83 mcg/mL

There was no effect of food on the absorption of acyclovir (n = 6); therefore, acyclovir capsules and tablets may be administered with or without food.

The only known urinary metabolite is 9-[(carboxymethoxy)methyl]guanine.

Special Populations: Adults with Impaired Renal Function: The half-life and total body clearance of acyclovir are dependent on renal function. A dosage adjustment is recommended for patients with reduced renal function (See DOSAGE AND ADMINISTRATION).

Geriatrics: Acyclovir plasma concentrations are higher in geriatric patients compared to younger adults, in part due to age-related changes in renal function. Dosage reduction may be required in geriatric patients with underlying renal impairment (See PRECAUTIONS: Geriatric Use).

Pediatrics: In general, the pharmacokinetics of acyclovir in pediatric patients is similar to that of adults. Mean half-life after oral doses of 300 mg/m^2 and 600 mg/m^2 in pediatric patients aged 7 months to 7 years was 2.6 hours (range 1.59 to 3.74 hours).

Drug Interactions: Co-administration of probenecid with intravenous acyclovir has been shown to increase the mean acyclovir half-life and the area under the concentration-time curve. Urinary excretion and renal clearance were correspondingly reduced.

Clinical Trials

Initial Genital Herpes: Double-blind, placebo-controlled studies have demonstrated that orally administered acyclovir significantly reduced the duration of acute infection and duration of lesion healing. The duration of pain and new lesion formation was decreased in some patient groups.

Recurrent Genital Herpes: Double-blind, placebo-controlled studies in patients with frequent recurrences (6 or more episodes per year) have shown that orally administered acyclovir given daily for 4 months to 10 years prevented or reduced the frequency and/or severity of recurrences in greater than 95% of patients.

In a study of patients who received acyclovir 400 mg twice daily for 3 years, 45%, 52%, and 63% of patients remained free of recurrences in the first, second, and third years, respectively. Serial analyses of the 3-month recurrence rates for the patients showed that 71% to 87% were recurrence free in each quarter.

Herpes Zoster Infections: In a double-blind, placebo-controlled study of immunocompetent patients with localized cutaneous zoster infection, acyclovir (800 mg 5 times daily for 10 days) shortened the times to lesion scabbing, healing, and complete cessation of pain, and reduced the duration of viral shedding and the duration of new lesion formation.

In a similar double-blind, placebo-controlled study, acyclovir (800 mg 5 times daily for 7 days) shortened the times to complete lesion scabbing, healing, and cessation of pain; reduced the duration of new lesion formation; and reduced the prevalence of localized zoster-associated neurologic symptoms (paresthesia, dysesthesia, or hyperesthesia).

Treatment was begun within 72 hours of rash onset and was most effective if started within the first 48 hours.

Adults greater than 50 years of age showed greater benefit.

Chickenpox: Three randomized, double-blind, placebo-controlled trials were conducted in 993 pediatric patients aged 2 to 18 years with chickenpox. All patients were treated within 24 hours after the onset of rash. In 2 trials, acyclovir was administered at 20 mg/kg 4 times daily (up to 3,200 mg per day) for 5 days. In the third trial, doses of 10, 15, or 20 mg/kg were administered 4 times daily for 5 to 7 days. Treatment with acyclovir shortened the time to 50% healing; reduced the maximum number of lesions; reduced the median number of vesicles; decreased the median number of residual lesions on day 28; and decreased the proportion of patients with fever, anorexia, and lethargy by day 2. Treatment with acyclovir did not affect varicella-zoster virus-specific humoral or cellular immune responses at 1 month or 1 year following treatment.

INDICATIONS AND USAGE

Herpes Zoster Infections: Acyclovir capsules, USP and acyclovir tablets, USP are indicated for the acute treatment of herpes zoster (shingles).

Genital Herpes: Acyclovir capsules, USP and acyclovir tablets, USP are indicated for the treatment of initial episodes and the management of recurrent episodes of genital herpes.

Chickenpox: Acyclovir capsules, USP and acyclovir tablets, USP are indicated for the treatment of chickenpox (varicella).

CONTRAINDICATIONS

Acyclovir is contraindicated for patients who develop hypersensitivity to acyclovir or valacyclovir.

WARNINGS

Acyclovir capsules and tablets are intended for oral ingestion only. Renal failure, in some cases resulting in death, has been observed with acyclovir therapy (See ADVERSE REACTIONS: Observed During Clinical Practice and OVERDOSAGE). Thrombotic thrombocytopenic purpura/hemolytic uremic syndrome (TTP/HUS), which has resulted in death, has occurred in immunocompromised patients receiving acyclovir therapy.

PRECAUTIONS

Dosage adjustment is recommended when administering acyclovir to patients with renal impairment (See DOSAGE AND ADMINISTRATION). Caution should also be exercised when administering acyclovir to patients receiving potentially nephrotoxic agents since this may increase the risk of renal dysfunction and/or the risk of reversible central nervous system symptoms such as those that have been reported in patients treated with intravenous acyclovir. Adequate hydration should be maintained.

Information for Patients

Patients are instructed to consult with their physician if they experience severe or troublesome adverse reactions, they become pregnant or intend to become pregnant, they intend to breastfeed while taking orally administered acyclovir, or they have any other questions.

Patients should be advised to maintain adequate hydration.

Herpes Zoster: There are no data on treatment initiated more than 72 hours after onset of the zoster rash. Patients should be advised to initiate treatment as soon as possible after a diagnosis of herpes zoster.

Genital Herpes Infections: Patients should be informed that acyclovir is not a cure for genital herpes. There are no data evaluating whether acyclovir will prevent transmission of infection to others. Because genital herpes is a sexually transmitted disease, patients should avoid contact with lesions or intercourse when lesions and/or symptoms are present to avoid infecting partners. Genital herpes can also be transmitted in the absence of symptoms through asymptomatic viral shedding. If medical management of a genital herpes recurrence is indicated, patients should be advised to initiate therapy at the first sign or symptom of an episode.

Chickenpox: Chickenpox in otherwise healthy children is usually a self-limited disease of mild to moderate severity. Adolescents and adults tend to have more severe disease. Treatment was initiated within 24 hours of the typical chickenpox rash in the controlled studies, and there is no information regarding the effects of treatment begun later in the disease course.

Drug Interactions

See CLINICAL PHARMACOLOGY: Pharmacokinetics.

Carcinogenesis, Mutagenesis, Impairment of Fertility

The data presented below include references to peak steady-state plasma acyclovir concentrations observed in humans treated with 800 mg given orally 5 times a day (dosing appropriate for treatment of herpes zoster) or 200 mg given orally 5 times a day (dosing appropriate for treatment of genital herpes). Plasma drug concentrations in animal studies are expressed as multiples of human exposure to acyclovir at the higher and lower dosing schedules (See CLINICAL PHARMACOLOGY: Pharmacokinetics).

Acyclovir was tested in lifetime bioassays in rats and mice at single daily doses of up to 450 mg/kg administered by gavage. There was no statistically significant difference in the incidence of tumors between treated and control animals, nor did acyclovir shorten the latency of tumors. Maximum plasma concentrations were 3 to 6 times human levels in the mouse bioassay and 1 to 2 times human levels in the rat bioassay.

Acyclovir was tested in 16 in vitro and in vivo genetic toxicity assays. Acyclovir was positive in 5 of the assays.

Acyclovir did not impair fertility or reproduction in mice (450 mg/kg/day, p.o.) or in rats (25 mg/kg/day, s.c.). In the mouse study, plasma levels were 9 to 18 times human levels, while in the rat study, they were 8 to 15 times human levels. At higher doses (50 mg/kg/day, s.c.) in rats and rabbits (11 to 22 and 16 to 31 times human levels, respectively) implantation efficacy, but not litter size, was decreased. In a rat peri- and post-natal study at 50 mg/kg/day, s.c., there was a statistically significant decrease in group mean numbers of corpora lutea, total implantation sites, and live fetuses.

No testicular abnormalities were seen in dogs given 50 mg/kg/day, IV for 1 month (21 to 41 times human levels) or in dogs given 60 mg/kg/day orally for 1 year (6 to 12 times human levels). Testicular atrophy and aspermatogenesis were observed in rats and dogs at higher dose levels.

Pregnancy

Teratogenic Effects: Pregnancy Category B. Acyclovir administered during organogenesis was not teratogenic in the mouse (450 mg/kg/day, p.o.), rabbit (50 mg/kg/day, s.c. and IV), or rat (50 mg/kg/day, s.c.). These exposures resulted in plasma levels 9 and 18, 16 and 106, and 11 and 22 times, respectively, human levels.

There are no adequate and well-controlled studies in pregnant women. A prospective epidemiologic registry of acyclovir use during pregnancy was established in 1984 and completed in April 1999. There were 749 pregnancies followed in women exposed to systemic acyclovir during the first trimester of pregnancy resulting in 756 outcomes. The occurrence rate of birth defects approximates that found in the general population.

However, the small size of the registry is insufficient to evaluate the risk for less common defects or to permit reliable or definitive conclusions regarding the safety of acyclovir in pregnant women and their developing fetuses. Acyclovir should be used during pregnancy only if the potential benefit justifies the potential risk to the fetus.

Nursing Mothers

Acyclovir concentrations have been documented in breast milk in 2 women following oral administration of acyclovir and ranged from 0.6 to 4.1 times corresponding plasma levels. These concentrations would potentially expose the nursing infant to a dose of acyclovir up to 0.3 mg/kg per day. Acyclovir should be administered to a nursing mother with caution and only when indicated.

Pediatric Use

Safety and effectiveness of oral formulations of acyclovir in pediatric patients less than 2 years of age have not been established.

Geriatric Use

Of 376 subjects who received acyclovir in a clinical study of herpes zoster treatment in immunocompetent subjects ≥ 50 years of age, 244 were 65 and over while 111 were 75 and over. No overall differences in effectiveness for time to cessation of new lesion formation or time to healing were reported between geriatric subjects and younger adult subjects. The duration of pain after healing was longer in patients 65 and over. Nausea, vomiting, and dizziness were reported more frequently in elderly subjects. Elderly patients are more likely to have reduced renal function and require dose reduction. Elderly patients are also more likely to have renal or CNS adverse events. With respect to CNS adverse events observed during clinical practice, somnolence, hallucinations, confusion, and coma were reported more frequently in elderly patients (See CLINICAL PHARMACOLOGY, ADVERSE REACTIONS: Observed During Clinical Practice, and DOSAGE AND ADMINISTRATION).

ADVERSE REACTIONS

Herpes Simplex: Short-Term Administration: The most frequent adverse events reported during clinical trials of treatment of genital herpes with acyclovir 200 mg administered orally 5 times daily every 4 hours for 10 days were nausea and/or vomiting in 8 of 298 patient treatments (2.7%). Nausea and/or vomiting occurred in 2 of 287 (0.7%) patients who received placebo.

Long-Term Administration: The most frequent adverse events reported in a clinical trial for the prevention of recurrences with continuous administration of 400 mg (two 200 mg capsules) 2 times daily for 1 year in 586 patients treated with acyclovir were nausea (4.8%) and diarrhea (2.4%). The 589 control patients receiving intermittent treatment of recurrences with acyclovir for 1 year reported diarrhea (2.7%), nausea (2.4%), and headache (2.2%).

Herpes Zoster: The most frequent adverse event reported during 3 clinical trials of treatment of herpes zoster (shingles) with 800 mg of oral acyclovir 5 times daily for 7 to 10 days in 323 patients was malaise (11.5%). The 323 placebo recipients reported malaise (11.1%).

Chickenpox: The most frequent adverse event reported during 3 clinical trials of treatment of chickenpox with oral acyclovir at doses of 10 to 20 mg/kg 4 times daily for 5 to 7 days or 800 mg 4 times daily for 5 days in 495 patients was diarrhea (3.2%). The 498 patients receiving placebo reported diarrhea (2.2%).

Observed During Clinical Practice: In addition to adverse events reported from clinical trials, the following events have been identified during post-approval use of acyclovir. Because they are reported voluntarily from a population of unknown size, estimates of frequency cannot be made. These events have been chosen for inclusion due to either their seriousness, frequency of reporting, potential causal connection to acyclovir, or a combination of these factors.

General: Anaphylaxis, angioedema, fever, headache, pain, peripheral edema.

Nervous: Aggressive behavior, agitation, ataxia, coma, confusion, decreased consciousness, delirium, dizziness, dysarthria, encephalopathy, hallucinations, paresthesia, psychosis, seizure, somnolence, tremors. These symptoms may be marked, particularly in older adults or in patients with renal impairment (See PRECAUTIONS).

Digestive: Diarrhea, gastrointestinal distress, nausea.

Hematologic and Lymphatic: Anemia, leukocytoclastic vasculitis, leukopenia, lymphadenopathy, thrombocytopenia.

Hepatobiliary Tract and Pancreas: Elevated liver function tests, hepatitis, hyperbilirubinemia, jaundice.

Musculoskeletal: Myalgia.

Skin: Alopecia, erythema multiforme, photosensitive rash, pruritus, rash, Stevens-Johnson syndrome, toxic epidermal necrolysis, urticaria.

Special Senses: Visual abnormalities.

Urogenital: Renal failure, renal pain (may be associated with renal failure), elevated blood urea nitrogen, elevated creatinine, hematuria (See WARNINGS).

OVERDOSAGE

Overdoses involving ingestion of up to 100 capsules (20 g) have been reported. Adverse events that have been reported in association with overdosage include agitation, coma, seizures, and lethargy. Precipitation of acyclovir in renal tubules may occur when the solubility (2.5 mg/mL) is exceeded in the intratubular fluid. Overdosage has been reported following bolus injections or inappropriately high doses and in patients whose fluid and electrolyte balance were not properly monitored. This has resulted in elevated BUN and serum creatinine and subsequent renal failure. In the event of acute renal failure and anuria, the patient may benefit from hemodialysis until renal function is restored (See DOSAGE AND ADMINISTRATION).

DOSAGE AND ADMINISTRATION

Acute Treatment of Herpes Zoster: 800 mg every 4 hours orally, 5 times daily for 7 to 10 days.

Genital Herpes: Treatment of Initial Genital Herpes: 200 mg every 4 hours, 5 times daily for 10 days.

Chronic Suppressive Therapy for Recurrent Disease: 400 mg 2 times daily for up to 12 months, followed by re-evaluation. Alternative regimens have included doses ranging from 200 mg 3 times daily to 200 mg 5 times daily.

The frequency and severity of episodes of untreated genital herpes may change over time. After 1 year of therapy, the frequency and severity of the patient’s genital herpes infection should be re-evaluated to assess the need for continuation of therapy with acyclovir.

Intermittent Therapy: 200 mg every 4 hours, 5 times daily for 5 days. Therapy should be initiated at the earliest sign or symptom (prodrome) of recurrence.

Treatment of Chickenpox: Children (2 years of age and older): 20 mg/kg per dose orally 4 times daily (80 mg/kg/day) for 5 days. Children over 40 kg should receive the adult dose for chickenpox.

Adults and children over 40 kg: 800 mg 4 times daily for 5 days.

Intravenous acyclovir is indicated for the treatment of varicella-zoster infections in immunocompromised patients.

When therapy is indicated, it should be initiated at the earliest sign or symptom of chickenpox. There is no information about the efficacy of therapy initiated more than 24 hours after onset of signs and symptoms.

Patients with Acute or Chronic Renal Impairment: In patients with renal impairment, the dose of Acyclovir capsules and tablets should be modified as shown in Table 3:

Table 3: Dosage Modification for Renal Impairment
Normal Dosage | Creatinine Clearance | Adjusted Dosage Regimen
Regimen | (mL/min/1.73 m^2) | Dose(mg) | Dosing Interval
200 mg every | > 10 | 200 | every 4 hours, 5 times daily
4 hours | 0 to 10 | 200 | every 12 hours
400 mg every | > 10 | 400 | every 12 hours
12 hours | 0 to 10 | 200 | every 12 hours
800 mg every | > 25 | 800 | every 4 hours, 5 times daily
4 hours | 10 to 25 | 800 | every 8 hours
 | 0 to 10 | 800 | every 12 hours

Hemodialysis: For patients who require hemodialysis, the mean plasma half-life of acyclovir during hemodialysis is approximately 5 hours. This results in a 60% decrease in plasma concentrations following a 6-hour dialysis period. Therefore, the patient’s dosing schedule should be adjusted so that an additional dose is administered after each dialysis.

Peritoneal Dialysis: No supplemental dose appears to be necessary after adjustment of the dosing interval.

Bioequivalence of Dosage Forms: Acyclovir suspension was shown to be bioequivalent to acyclovir capsules (n = 20) and one acyclovir 800 mg tablet was shown to be bioequivalent to four acyclovir 200 mg capsules (n = 24).

HOW SUPPLIED

Acyclovir capsules, USP (white, opaque cap and body) containing 200 mg acyclovir, USP and printed with “RX 652” on both the cap and the body.

Bottle of 25 (NDC 21695-009-25)

Bottle of 30 (NDC 21695-009-30)

Acyclovir tablets, USP (white, oval-shaped, unscored) containing 800 mg acyclovir, USP and debossed with “RX 505” on one side.

Bottle of 21 (NDC 21695-011-21)

Bottle of 25 (NDC 21695-011-25)

Bottle of 30 (NDC 21695-011-30)

Bottle of 35 (NDC 21695-011-35)

Bottle of 40 (NDC 21695-011-40)

Acyclovir tablets, USP (white, oval-shaped, unscored) containing 400 mg acyclovir, USP and debossed with “RX 504” on one side.

Bottle of 20 (NDC 21695-010-20)

Bottle of 25 (NDC 21695-010-25)

Bottle of 30 (NDC 21695-010-30)

Bottle of 60 (NDC 21695-010-60)

Bottle of 90 (NDC 21695-010-90)

Store at 20 - 25° C (68 - 77° F) [See USP Controlled Room Temperature]. Protect from moisture.

Call your doctor for medical advice about side effects. You may report side effects to FDA at 1-800-FDA-1088.

Manufactured for:

Ranbaxy Pharmaceuticals Inc.

Jacksonville, FL 32257 USA

by: Ohm Laboratories Inc.

North Brunswick, NJ 08902 USA

April 2009

Repackaged By:

Rebel Distributors Corp

Thousand Oaks, CA 91320